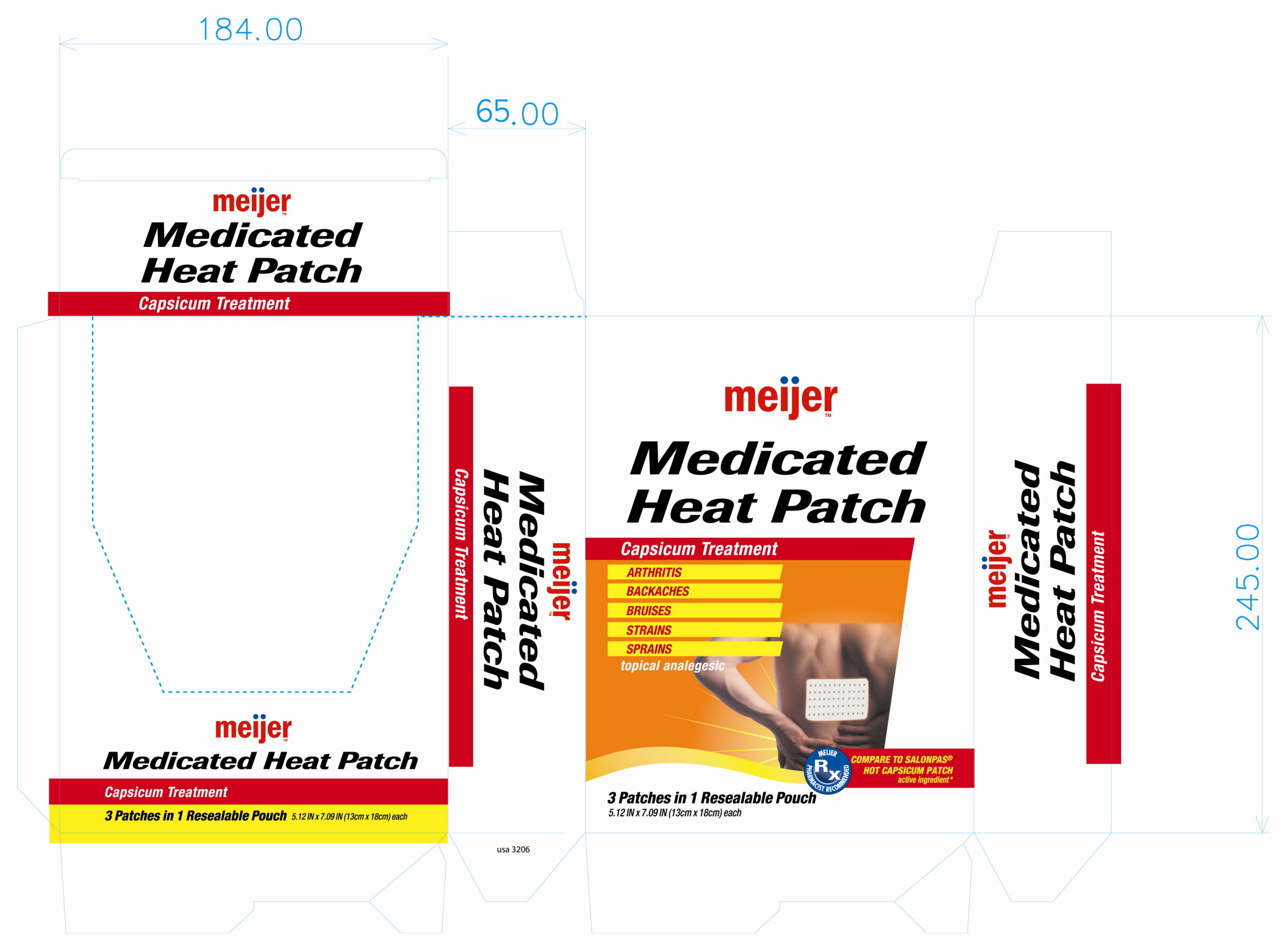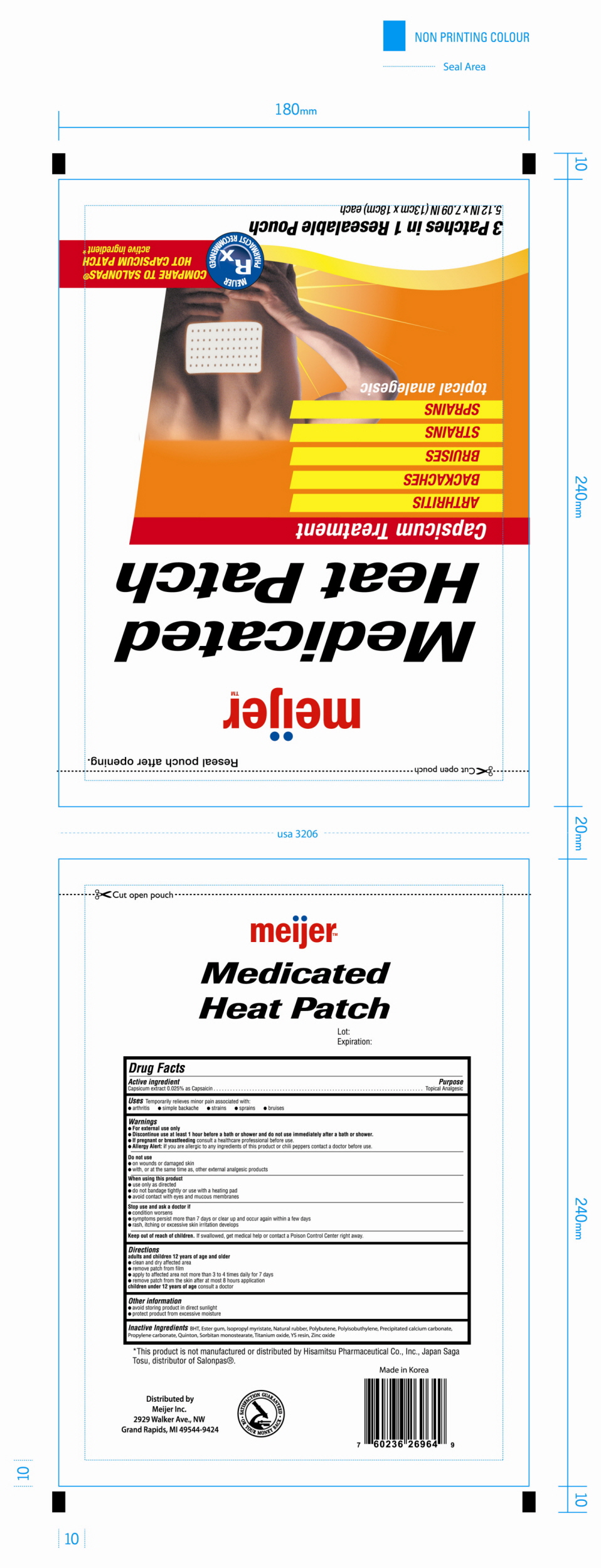 DRUG LABEL: Medicated Heat
NDC: 55264-269 | Form: PATCH
Manufacturer: United Exchange Corporation
Category: otc | Type: HUMAN OTC DRUG LABEL
Date: 20100517

ACTIVE INGREDIENTS: Capsaicin 0.6 mg/1 1

Capsicum Treatment (Medicated Heat Patch)

Active Ingredient

Capsicum extract 0.025 % as Capsaicin

Purpose

Topical Analgesic

Uses

Temporarily relieves minor pain associated with:

- arthritis
- simple backache
- strains
- sprains
- bruises

Warnings

- For external use only.
- Discontinue use at least 1 hour before a bath or shower and do not use immediately after a bath or shower.
- If pregnant or breastfeeding consult a healthcare professional before use.
- Allergy Alert: if you are allergic to any ingredients of this product or chili peppers contact a doctor before use.

Do not use

- on wounds or damage skin
- with, or at the same time as, other external analgesic products

When using this product

- use only as directed
- do not bandage tightly or use with a heating pad
- avoid contact with eyes and mucous membranes

Stop use and ask a doctor if

- condition worsens
- symptoms persist more than 7 days or clear up and occur again within a few days
- rash, itching or excessive skin irritation develops

Keep out of reach of children.

If swallowed, get medical help or contact a Poison Control Center right away.

Directions

adults and children under 12 years of age and older

- clean and dray affected area
- remove patch from film
- apply to affected area not more than 3 to 4 times daily for 7 days
- remove patch from the skin after at most 8 hours application

children under 12 year of age consult a doctor

Other information

- avoid storing product in direct sunlight
- protect product from excessive moisture

Inactive Ingredients

BHT, Ester gum, Isopropyl myristate, Natural rubber, Polybutene, Polyisobuthylene, Precipitated calcium carbonate, Propylene carbonate, Quinton, Sorbitan monostearate, Titanium oxide, YS resin, Zinc oxide